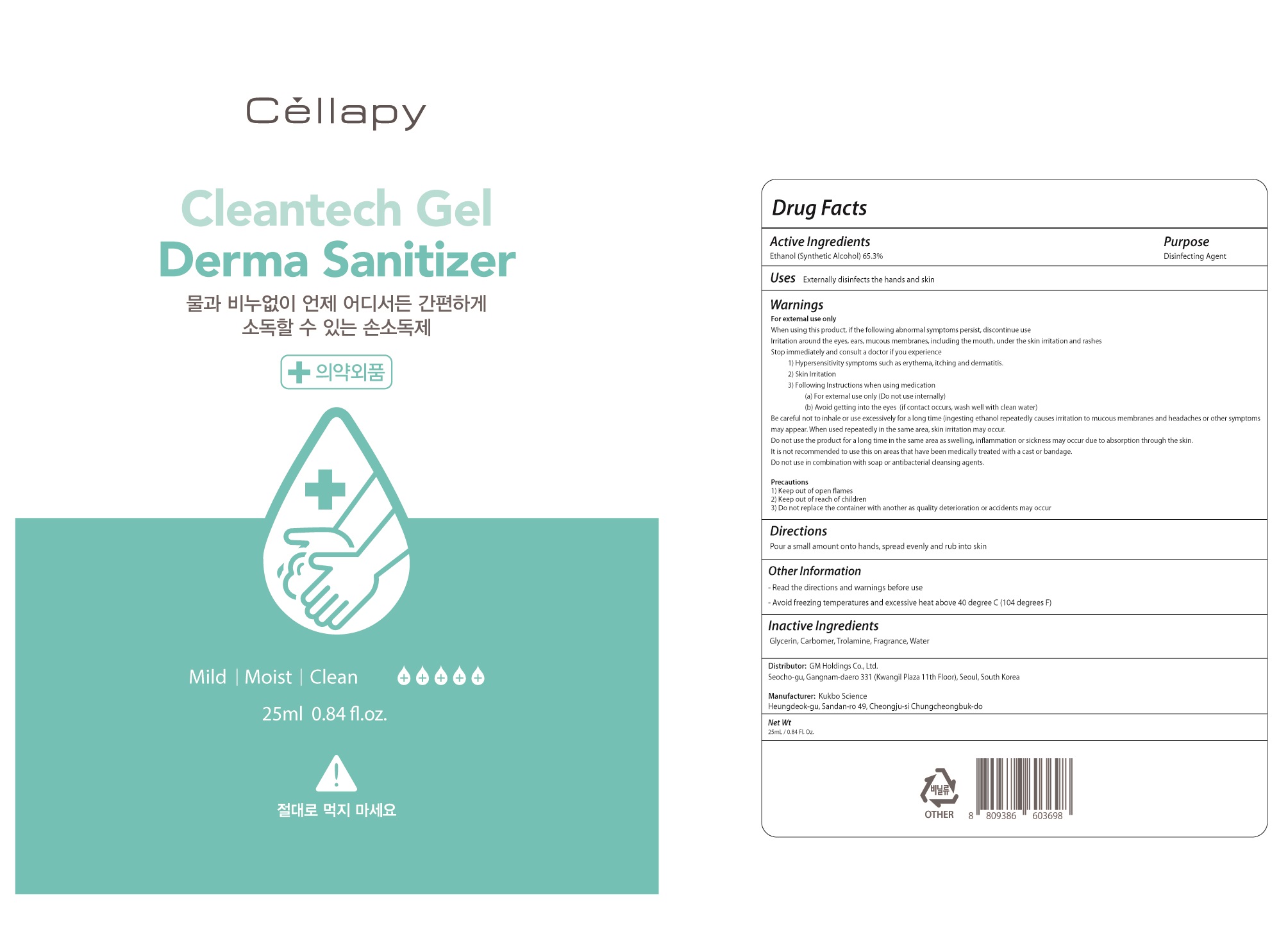 DRUG LABEL: Cellapy Dr Sanitizer 25mL
NDC: 69278-111 | Form: GEL
Manufacturer: GM Holdings Co., Ltd
Category: otc | Type: HUMAN OTC DRUG LABEL
Date: 20200328

ACTIVE INGREDIENTS: ALCOHOL 16.32 g/25 mL
INACTIVE INGREDIENTS: GLYCERIN; CARBOMER HOMOPOLYMER, UNSPECIFIED TYPE; Trolamine; Water

Drug Facts

ACTIVE INGREDIENT

ACTIVE INGREDIENT: Ethanol (Synthetic Alcohol 65.3%)

INACTIVE INGREDIENT

Glycerin, Carbomer, Trolamine, Fragrance, Water

PURPOSE

PURPOSE: Disinfecting Agent

KEEP OUT OF REACH OF CHILDREN

KEEP OUT OF REACH OF THE CHILDREN

Uses:

Uses : Externally disinfects the hands and skin

WARNINGS

For external use only
When using this product if following abnormal symptoms persist, discontinue use
1) Irritation around the eyes, ears, mucous membranes, including the mouth, under the skin irritation and rashes

Stop immediately and consult a doctor if you experience
1) Hypersensitivity symptoms such as erythema, itching and dermatitis.
2) Skin Irritation
3) Following Instructions when using medication
1) For external use only (Do not use internally)
2) Avoid getting into the eyes
(if contact occurs, wash well with clean water
Be careful to not inhale or use excessively for a long time (ingesting ethanol repeatedly causes irritation to mucous membranes and headaches or other symptoms may appear. When used repeatedly in the same area, skin irritation may occur.
Do not use the product for a long time in the same area as swelling, inflammation may occur or sickness due to absorption through the skin.
It is not recommended to use this one areas that have been medically treated with a cast or bandage.
Do not use in combination with soap or antibacterial cleansing agents.

Precautions
1) Keep out of open flames
2) Keep out of reach of children
3) Do not replace the container with another as quality deterioration or accidents may occur

Directions

Pour a small amount onto hands, spready evenly and rub into skin